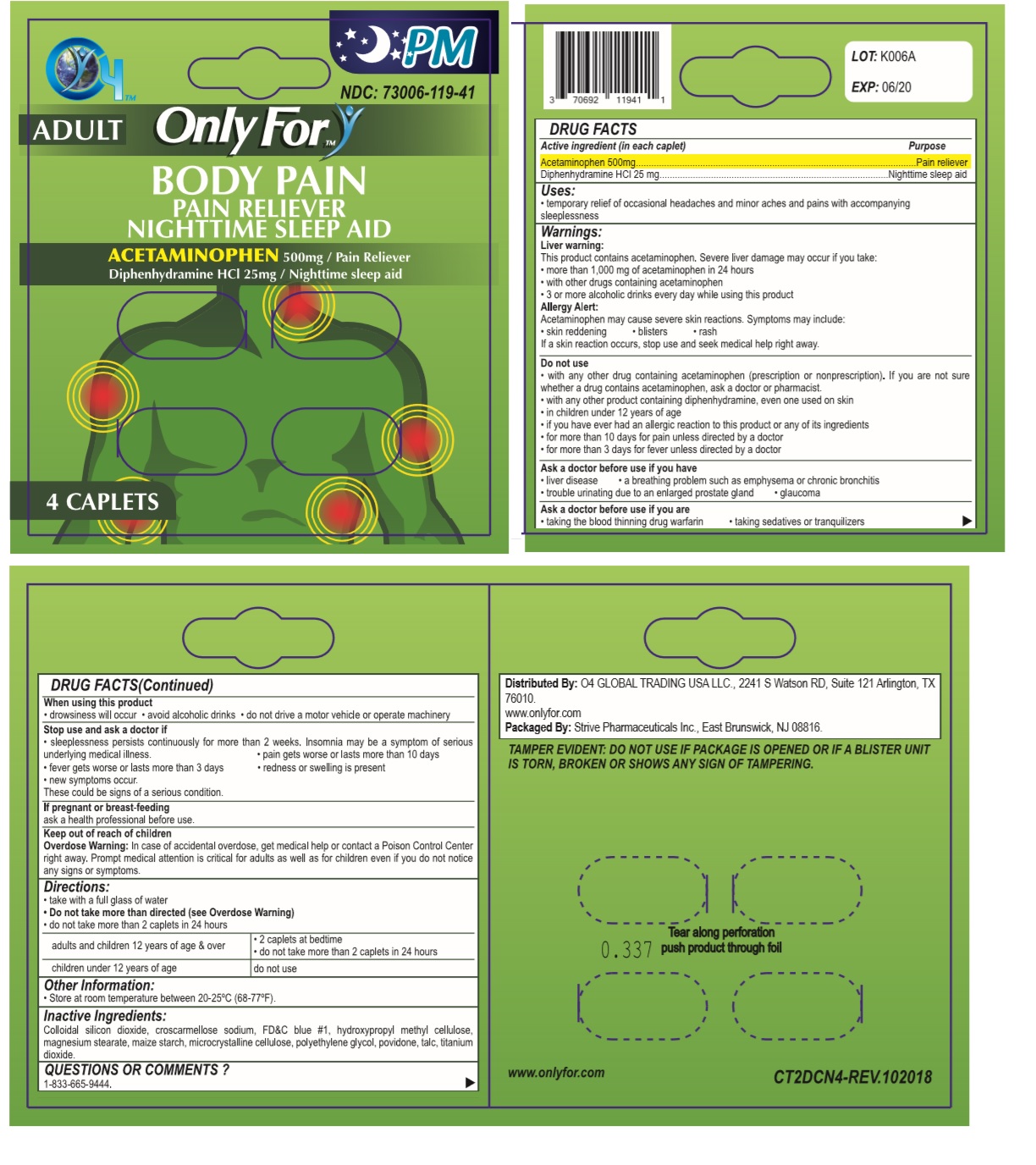 DRUG LABEL: Only For
NDC: 73006-119 | Form: TABLET
Manufacturer: O4 Global Trading Usa, Llc 
Category: otc | Type: HUMAN OTC DRUG LABEL
Date: 20190429

ACTIVE INGREDIENTS: ACETAMINOPHEN 500 mg/1 1; DIPHENHYDRAMINE HYDROCHLORIDE 25 mg/1 1
INACTIVE INGREDIENTS: SILICON DIOXIDE; CROSCARMELLOSE SODIUM; FD&C BLUE NO. 1--ALUMINUM LAKE; HYPROMELLOSE 2910 (5 MPA.S); MAGNESIUM PALMITOSTEARATE; STARCH, CORN; MICROCRYSTALLINE CELLULOSE 101; POLYETHYLENE GLYCOL 400; POVIDONE, UNSPECIFIED; TALC; TITANIUM DIOXIDE

Only For - BODY PAIN

Active ingredient (in each caplet)

Acetaminophen 500 mg

Diphenhydramine HCl 25 mg

Purpose

Pain reliever

Nighttime sleep aid

Uses:

- temporary relief of occasional headaches and minor aches and pains with accompanying sleeplessness

Warnings:

Liver warning:

This product contains acetaminophen. Severe liver damage may occur if you take:

- more than 1,000 mg of acetaminophen in 24 hours
- with other drugs containing acetaminophen
- 3 or more alcoholic drinks everyday while using this product

Allergy Alert:

Acetaminophen may cause severe skin reactions. Symptoms may include:

• skin reddening • blisters • rash

If a skin reaction occurs, stop use and seek medical help right away.

Do not use

- with any other drug containing acetaminophen (prescription or nonprescription). If you are not sure whether a drug contains acetaminophen, ask a doctor or pharmacist.
- with any other product containing diphenhydramine, even one used on skin
- in children under 12 years of age
- if you have ever had any allergic reaction to this product or any of its ingredients
- for more than 10 days for pain unless directed by a doctor
- for more than 3 days for fever unless directed by a doctor

Ask a doctor before use if you have

• liver disease • a breathing problem such as emphysema or chronic bronchitis

• trouble urinating due to an enlarged prostate gland • glaucoma

Ask a doctor before use if you are

• taking the blood thinning drug warfarin • taking sedatives or tranquilizers

When using this product

• drowsiness will occur • avoid alcoholic drinks • do not drive a motor vehicle or operate machinery

Stop use and ask a doctor if

• sleeplessness persists continously for more than 2 weeks. Insomnia may be a symptom of serious underlying medical illness. • pain gets worse or lasts more than 10 days

• fever gets worse or last more than 3 days • redness or swelling is present

• new symptoms occur.

These could be signs of a serious condition.

If pregnant or breast-feeding
ask a health professional before use.

Keep out of reach of children

Overdose Warning: In case of accidental overdose, get medical help or contact a Poison Control Center right away. Prompt medical attention is critical for adults as well as for children even if you do not notice any signs or symptoms.

Directions:

- take with a full glass of water
- Do not take more than directed (see Overdose Warning)
- do not take more than 2 caplets in 24 hours

adults and children 12 years of age and over | - 2 caplets at bedtime - do not take more than 2 caplets in 24 hours
children under 12 years of age | do not use

Other Information:

- Store at room temperature between 20-25°C (68-77°F).

Inactive Ingredients:

Colloidal silicon dioxide, croscarmellose sodium, FD&C blue #1, hydroxypropyl methyl cellulose, magnesium stearate, maize starch, microcrystalline cellulose, polyethylene glycol, povidone, talc, titanium dioxide.

Questions Or Comments ?

1-833-665-9444.

NDC: 73006-119-41

Distributed By: O4 GLOBAL TRADING USA LLC., 2241 S Watson RD, Suite 121 Arlington, TX 76010.

www.onlyfor.com

Packaged By: Strive Pharmaceuticals Inc., East Brunswick, NJ 08816.

TAMPER EVIDENT: DO NOT USE IF PACKAGE IS OPENED OR IF A BLISTER UNIT IS TORN, BROKEN OR SHOWS ANY SIGN OF TAMPERING.

Tear along perforation push product through foil